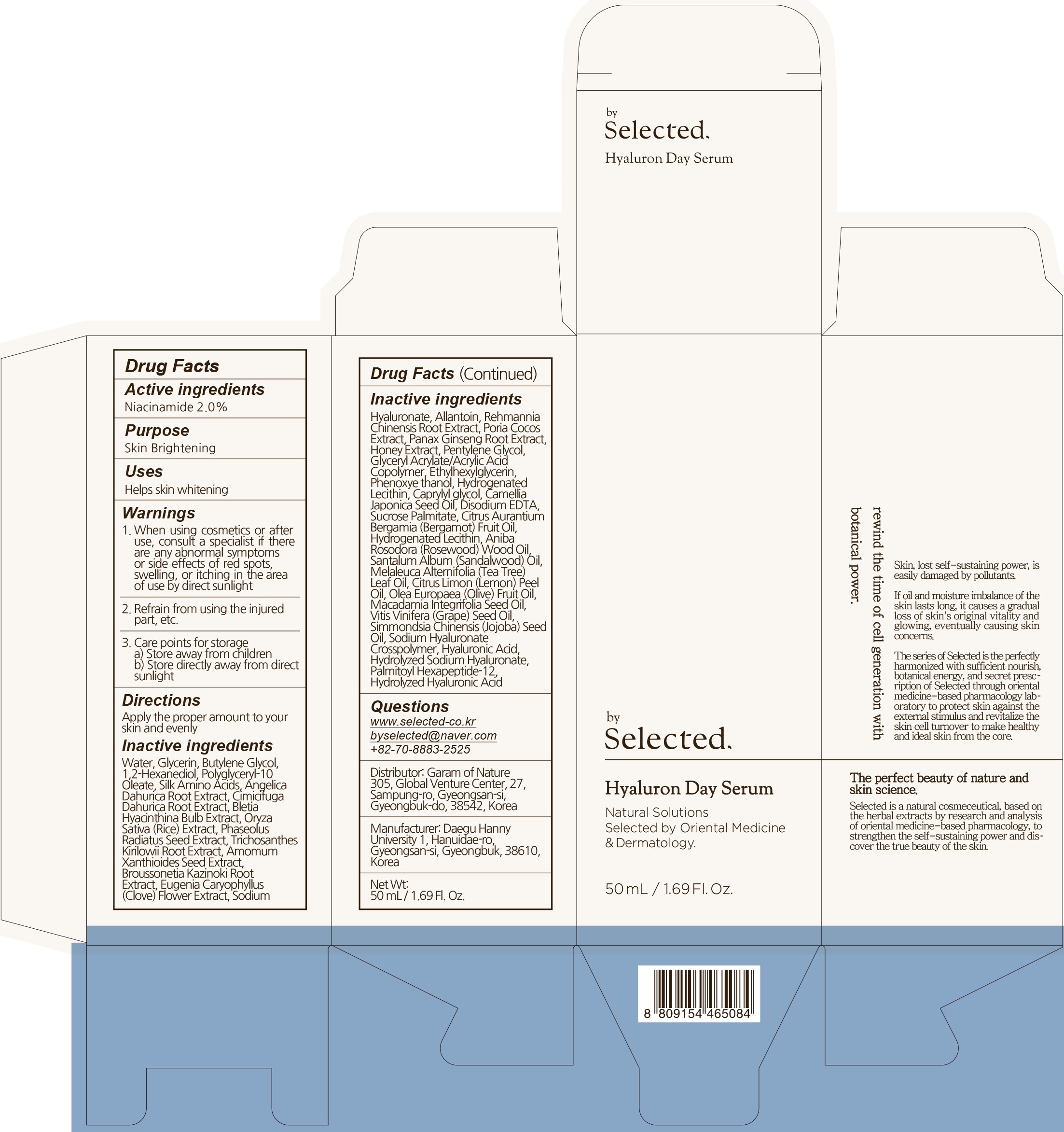 DRUG LABEL: by selected hyaluron day serum
NDC: 73509-030 | Form: LIQUID
Manufacturer: Garam Of Nature
Category: otc | Type: HUMAN OTC DRUG LABEL
Date: 20191217

ACTIVE INGREDIENTS: Niacinamide 1.00 g/50 mL
INACTIVE INGREDIENTS: Water; Glycerin

ACTIVE INGREDIENT

Active ingredients: Niacinamide 2.0%

INACTIVE INGREDIENT

Inactive ingredients:

Water, Glycerin, Butylene Glycol, 1,2-Hexanediol, Polyglyceryl-10 Oleate, Silk Amino Acids, Angelica Dahurica Root Extract, Cimicifuga Dahurica Root Extract, Bletia Hyacinthina Bulb Extract, Oryza Sativa (Rice) Extract, Phaseolus Radiatus Seed Extract, Trichosanthes Kirilowii Root Extract, Amomum Xanthioides Seed Extract, Broussonetia Kazinoki Root Extract, Eugenia Caryophyllus (Clove) Flower Extract, Sodium Hyaluronate, Allantoin, Rehmannia Chinensis Root Extract, Poria Cocos Extract, Panax Ginseng Root Extract, Honey Extract, Pentylene Glycol, Glyceryl Acrylate/Acrylic Acid Copolymer, Ethylhexylglycerin, Phenoxyethanol, Hydrogenated Lecithin, Caprylyl glycol, Camellia Japonica Seed Oil, Disodium EDTA, Sucrose Palmitate, Citrus Aurantium Bergamia (Bergamot) Fruit Oil, Hydrogenated Lecithin, Aniba Rosodora (Rosewood) Wood Oil, Santalum Album (Sandalwood) Oil, Melaleuca Alternifolia (Tea Tree) Leaf Oil, Citrus Limon (Lemon) Peel Oil, Olea Europaea (Olive) Fruit Oil, Macadamia Integrifolia Seed Oil, Vitis Vinifera (Grape) Seed Oil, Simmondsia Chinensis (Jojoba) Seed Oil, Sodium Hyaluronate Crosspolymer, Hyaluronic Acid, Hydrolyzed Sodium Hyaluronate, Palmitoyl Hexapeptide-12, Hydrolyzed Hyaluronic Acid

PURPOSE

Purpose: Skin Brightening

WARNINGS

1. In case of having following symptoms after using this, you're advised to stop using it immediately. If you keep using it, the symptoms will get worse and need to consult a dermatologist 1) In case of having problems such as red rash, swollenness, itching, stimulation during usage 2) In case of having the same symptoms above on the part you put this product on by direct sunlight 2. You are banned to use it on the part where you have a scar, eczema, or dermatitis 3. In case of getting it into your eyes, you have to wash it immediately 4. Caution for treatment and keeping 1) Tighten the lid after using it 2) Keep it out of infants or children's reach 3) Don't keep it in the place where the temperature is extremely hot or low and exposed to the direct sunlight

KEEP OUT OF REACH OF CHILDREN

Keep it out of infants or children's reach

Uses

Helps skin whitening.

Directions

Apply the proper amount to your skin and evenly

QUESTIONS

www.selected-co.kr
byselected@naver.com
+82-70-8883-2525